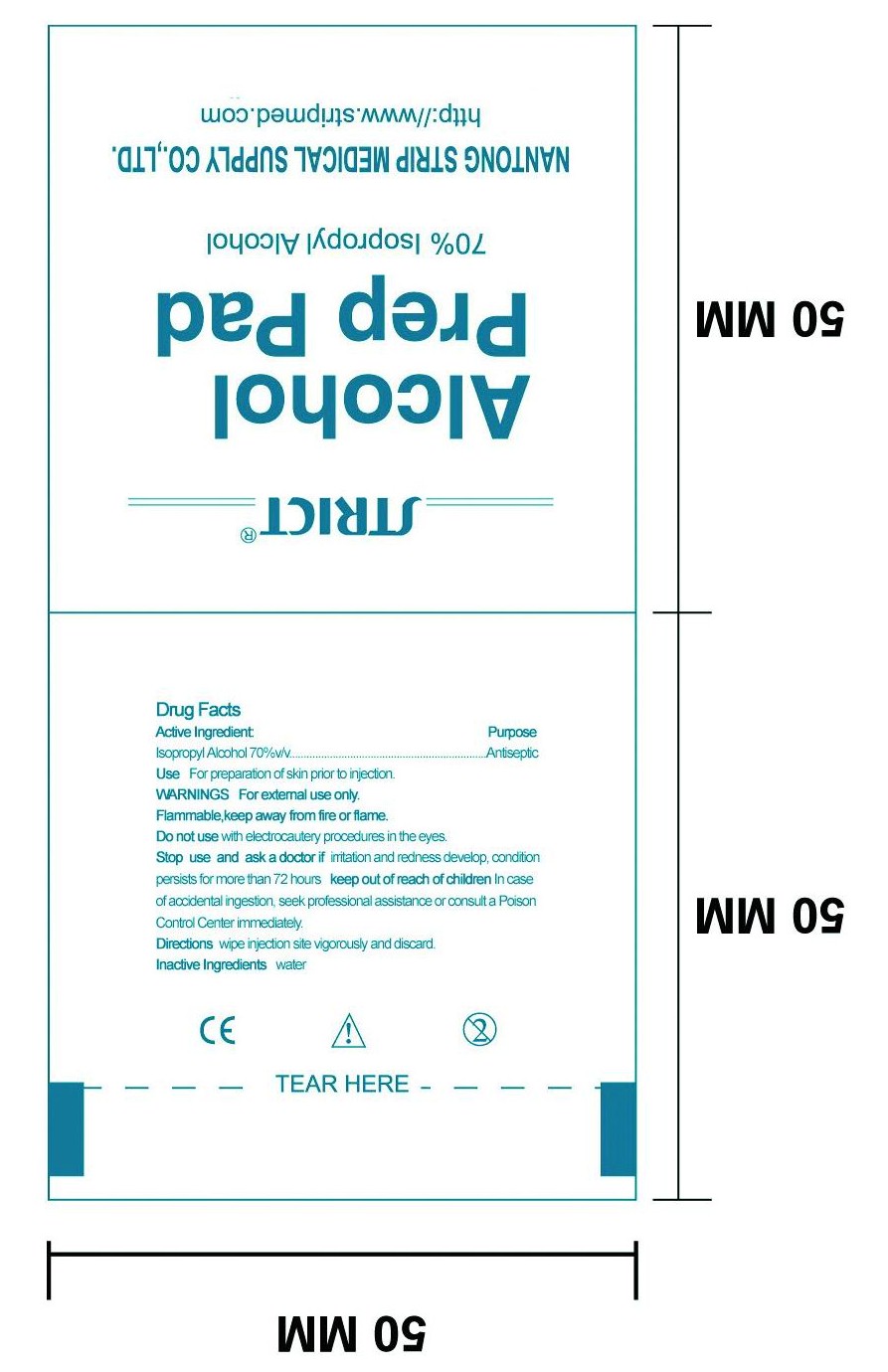 DRUG LABEL: Alcohol Prep Pad
NDC: 35617-394 | Form: SWAB
Manufacturer: NANTONG STRIP MEDICAL SUPPLY CO.,LTD.
Category: otc | Type: HUMAN OTC DRUG LABEL
Date: 20100525

ACTIVE INGREDIENTS: ISOPROPYL ALCOHOL 0.7 mL/1 1
INACTIVE INGREDIENTS: WATER 0.3 mL/1 1

Drug Facts

Active Ingredient

Isopropyl Alcohol 70%

Purpose

Antiseptic

Use

For preparation of skin prior to injection.

Warnning

For External use only.

Flammable,keep away from fire or flame.

Do not use with electrocautery procedures in eyes.

Stop use and ask a doctor if irritation and redness develop,condition persists for more than 72 hours .

Keep out of reach of children in case of accidental ingestion,seek professional assistance or consult a Poison Control Center immediately.

Directions

Wipe injection site vigorously and discard.

Inactive Ingredients

Inactive Ingredients: Water

PACKAGE LABEL

Enter section text here